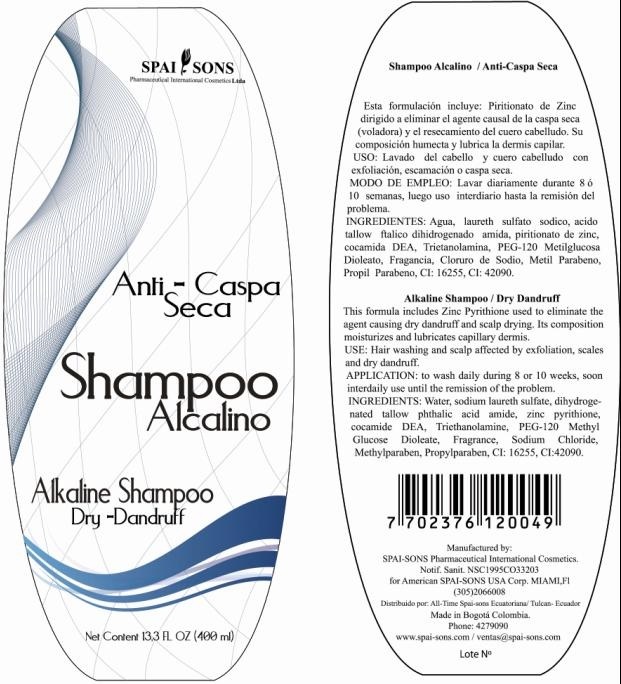 DRUG LABEL: SPAI-SONS 
NDC: 66854-017 | Form: SHAMPOO
Manufacturer: SPAI-SONS PHARMACEUTICAL INTERNATIONAL COSMETICS
Category: otc | Type: HUMAN OTC DRUG LABEL
Date: 20120605

ACTIVE INGREDIENTS: PYRITHIONE ZINC 1 mL/100 mL
INACTIVE INGREDIENTS: WATER; SODIUM LAURETH SULFATE; DIHYDROGENATED TALLOW PHTHALIC ACID AMIDE; COCO DIETHANOLAMIDE; TROLAMINE; PEG-120 METHYL GLUCOSE DIOLEATE; SODIUM CHLORIDE; METHYLPARABEN; PROPYLPARABEN; PONCEAU 4R; FD&C BLUE NO. 1

SPAI-SONS SHAMPOO ALCALINO ANTI CASPA SECA / ALKALINE SHAMPOO DRY-DANDRUFF

ACTIVE INGREDIENT

This formula includes Zinc Pyrithione used to eliminate the agent causing dry dandruff and scalp drying.

PURPOSE

USE: Hair washing and scalp affected by exfoliation, scales and dry dandruff

KEEP OUT OF REACH OF CHILDREN

This product must be keep out reach of children.

INDICATIONS AND USAGE

This product is for topical appplication. Wash the hair with the shampoo in the shower.

WARNINGS

If this product is contact with eyes rinse immediately with water and consult your doctor

DOSAGE AND ADMINISTRATION

To wash daily during 8 or 10 weeks, soon interdaily use until the remission of the problem. This product is for topical application

INACTIVE INGREDIENT

This composition moisturizes and lubricate capillary dermis

IMAGE OF THE LABEL